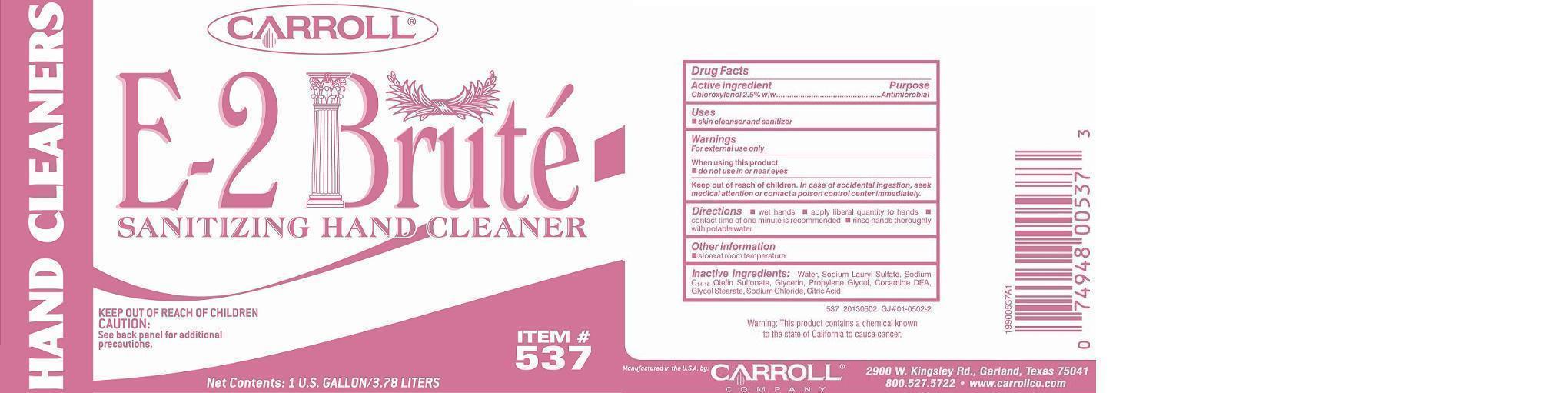 DRUG LABEL: PC537 E-2 BRUTE
NDC: 10685-537 | Form: SOAP
Manufacturer: CARROLL COMPANY
Category: otc | Type: HUMAN OTC DRUG LABEL
Date: 20180131

ACTIVE INGREDIENTS: CHLOROXYLENOL 25 g/1000 mL
INACTIVE INGREDIENTS: WATER; GLYCOL STEARATE; SODIUM LAURYL SULFATE; SODIUM C14-16 OLEFIN SULFONATE; COCO DIETHANOLAMIDE; PROPYLENE GLYCOL; GLYCERIN; CITRIC ACID MONOHYDRATE; SODIUM CHLORIDE

Active ingredient

Chloroxylenol 2.5% w/w

Purpose

Antimicrobial

Keep out of reach of children

In case of accidental ingestion, seek medical attention or contact a poison control center immediately.

Uses

- skin cleanser and sanitizer

Warnings

For external use only

When using this product

- do not use in or near eyes

Directions

 wet hands  apply liberal quantity to hands  contact time of one minute is recommended  rinse hands thoroughly with potable water.

Other information

 store at room temperature

Inactive ingredients:

Water, Sodium Lauryl Sulfate, Sodium C14-16 Olefin Sulfonate, Glycerin, Propylene Glycol, Cocamide DEA, Glycol Stearate, Sodium Chloride, Citric Acid.